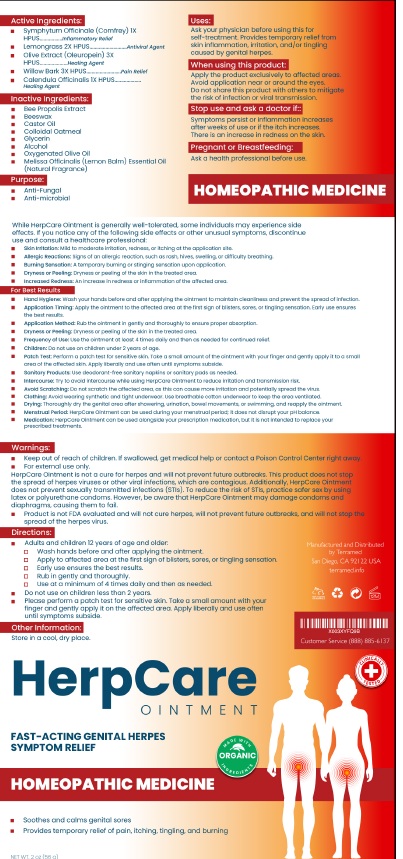 DRUG LABEL: Terramed Just Think Comfort HerpCare Genital Herpes
NDC: 83004-022 | Form: OINTMENT
Manufacturer: Rida LLC
Category: homeopathic | Type: HUMAN OTC DRUG LABEL
Date: 20250320

ACTIVE INGREDIENTS: COMFREY ROOT 1 [hp_X]/56 g; CYMBOPOGON CITRATUS LEAF 2 [hp_X]/56 g; OLEUROPEIN 3 [hp_X]/56 g; WILLOW BARK 3 [hp_X]/56 g; CALENDULA OFFICINALIS WHOLE 1 [hp_X]/56 g
INACTIVE INGREDIENTS: PROPOLIS WAX; YELLOW WAX; CASTOR OIL; OATMEAL; GLYCERIN; ALCOHOL; OLIVE OIL; MELISSA OFFICINALIS SEED OIL

Active Ingredient

Symphytum officinale (Comfrey) 1X HPUS .............. .Inflammatory Relief
Lemongross 2X HPUS.. . ..........................................Antiviral Agent
Olive Extract (Oieuropein) 3X HPUS ............................ Healing Agent
Willow Bark 3X HPUS..... . ... Pain Relief
Calendula Officinalis 1X HPUS ....................................Healing Agent

Purpose

• Anti- Fungal
• Anti- microbial

Uses

Ask your physician before using this for self-treatment Provides temporary relief skin inflammation, irritation, and/ or tingling caused by genital herpes.

Warnings

- Keep out of reach of children. If swallowed, get medical help or contact a Poison Control
- For external use only.
- Herpcare Ointment is not a cure for herpes and will not prevent future outbreaks. This product does not stop the spread of herpes viruses or other viral infections, which are contagious. Additionally, Herpcare does not prevent sexually transmitted infections (STis). To reduce the risk of STis, practice safer sex latex or polyurethane condoms. However, be aware that HerpCare Ointment may damage condomas, diaphragms, causing them to fail.
- Product is not FDA evaluated and will not cure herpes, will not prevent future outbreaks, and will not stop the spread of the herpes virus.
- When using this product Apply the product exclusively to affected areas. Avoid application near or around the eyes. Do not share this product with others to mitigate the risk of infection or viral transmission.
- Stop use and ask a doctor Symptoms persist or inflammation increases after weeks of use or if the itch increases. There is an increase in redness on the skin.
- Pregnant or Breastfeeding : Ask a health professional before use.

Directions

Adults and children 12 years of age and older:

- Wash hand s before and after applying the ointment.
- Apply to affected area at the first sign of blisters, sores, or tingling sensation.
- Early use ensures the best results.
- Rub in gently and thoroughly.
- Use at a minimum of 4 times daily and then as needed.

Do not use on children less than 2 years.

Please perform a patch test for sensitive skin. Take a small am ount with your finger and gently apply it on the affected area.

Apply liberally and use often until symptoms subside.

Other Information

Store in a cool, dry place.

Inactive ingredients

Bee Propolis Extract, Beeswax, CastorOil, Colloidal Oatmeal, Glycerin, Alcohol, Oxygenated Olive Oil, Melissa Officinalis (lemon Balm) Essential Oil
(Natural Fragrance)